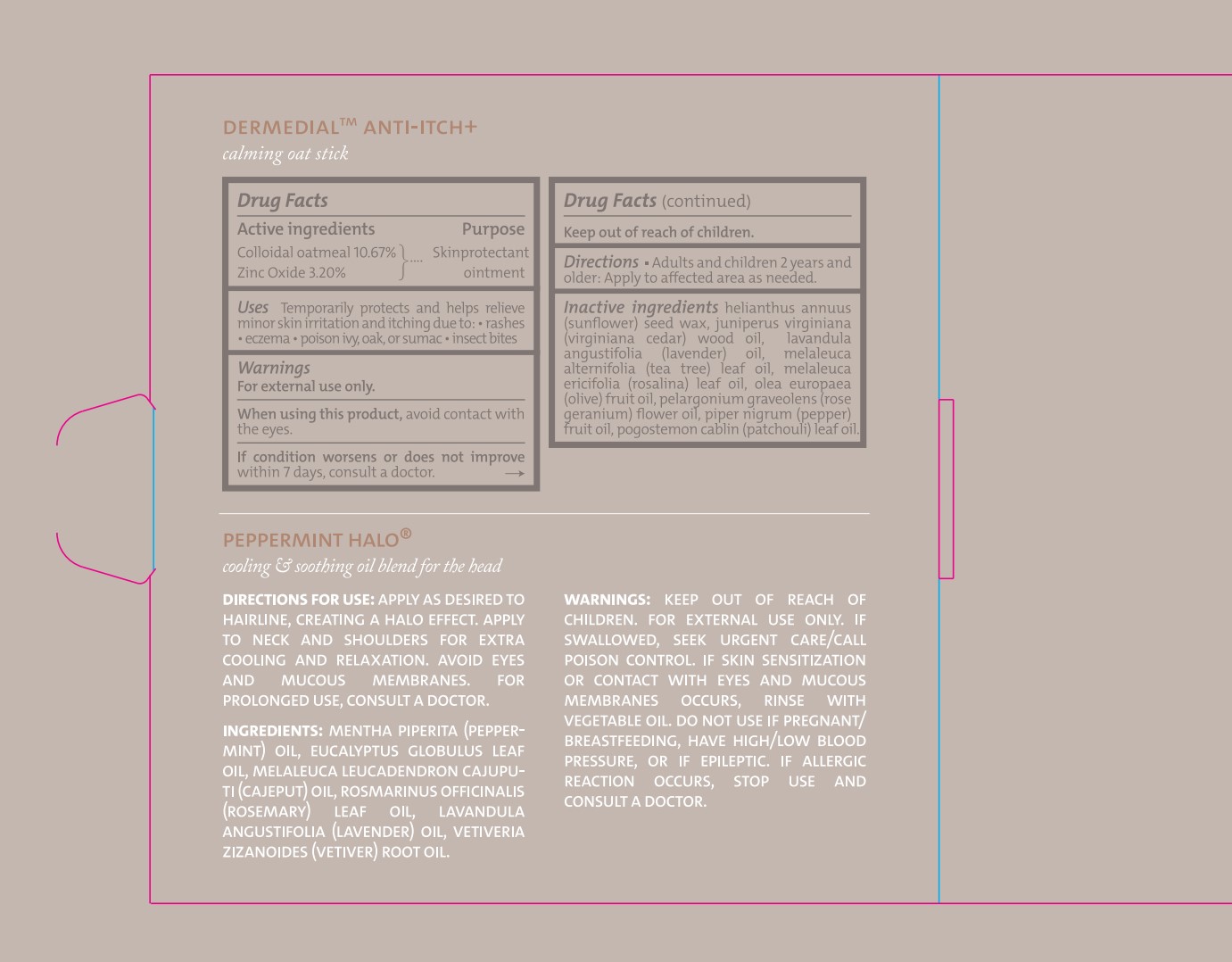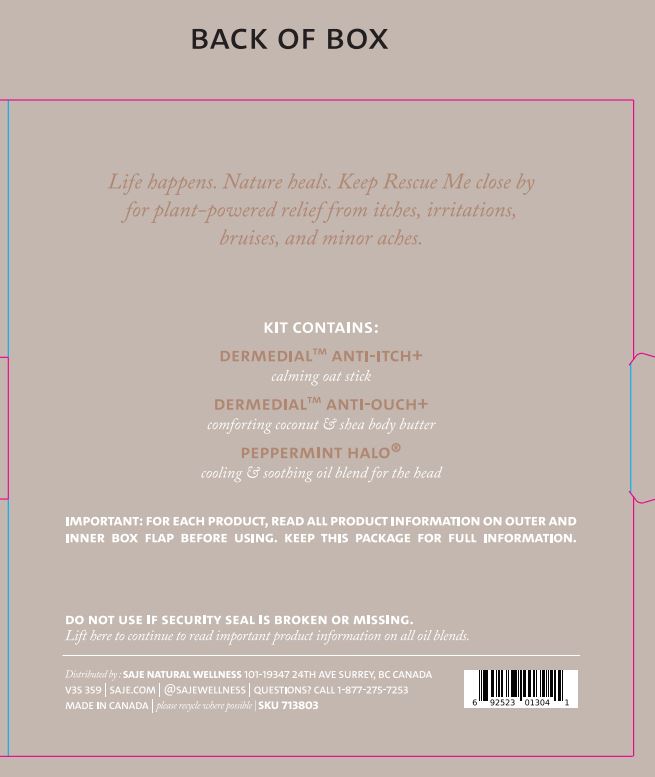 DRUG LABEL: DERMEDIAL Anti-Itch
NDC: 70983-029 | Form: OINTMENT
Manufacturer: Saje Natural Business Inc
Category: otc | Type: HUMAN OTC DRUG LABEL
Date: 20260113

ACTIVE INGREDIENTS: ZINC OXIDE 0.416 g/13 g; OATMEAL 1.3871 g/13 g
INACTIVE INGREDIENTS: HELIANTHUS ANNUUS (SUNFLOWER) SEED WAX; MELALEUCA ERICIFOLIA LEAF OIL; OLEA EUROPAEA (OLIVE) FRUIT OIL; POGOSTEMON CABLIN LEAF OIL; JUNIPERUS VIRGINIANA WOOD OIL; TEA TREE OIL; LAVENDER OIL; BLACK PEPPER OIL; PELARGONIUM GRAVEOLENS FLOWER OIL

Dermedial Anti-Itch + (13g)

ACTIVE INGREDIENT

Colloidal oatmeal 10.67%

Zinc oxide 3.20%

PURPOSE

Skin protectant ointment

INDICATIONS AND USAGE

Uses Temporarily protects and helps relieve minor skin irritation and itching due to:

- rashes
- eczema
- poison ivy, oak, or sumac
- insect bites

WARNINGS

For external use only. When using this product, avoid contact with the eyes. If condition worsens or does not improve within 7 days, consult a doctor. Keep out of reach of children.

WHEN USING

Avoid contact with the eyes.

ASK DOCTOR

If condition worsens or does not improve within 7 days, consult a doctor.

Keep out of reach of children.

DOSAGE AND ADMINISTRATION

Adults and children 2 years and older: Apply to affected area as needed.

INACTIVE INGREDIENT

helianthus annuus (sunflower) seed wax, juniperus virginiana (virginiana cedar) wood oil, lavandula angustifolia (lavender) oil, melaleuca alternifolia (tea tree) leaf oil, melaleuca ericifolia (rosalina) leaf oil, olea europaea (olive) fruit oil, pelargonium graveolens (rose geranium) flower oil, piper nigrum (pepper) fruit oil, pogostemon cablin (patchouli) leaf oil.

OTHER SAFETY INFORMATION

Important: For each product, read all product information on outer and inner box flap before using. Keep this package for full information.

Do not use if security seal is broken or missing.

DESCRIPTION

Dermedial Anti-Itch+

calming oat stick

QUESTIONS

Distributed by: Saje Natural Wellness 101-19347 24th Ave Surrey, BC V3S 3S9 | saje.com | @sajewellness | Questions? call 1-877-275-7253 | Made in Canada | Please recycle where possible | SKU 713803

PACKAGE LABEL

topical balm 0.45 oz | 13 g